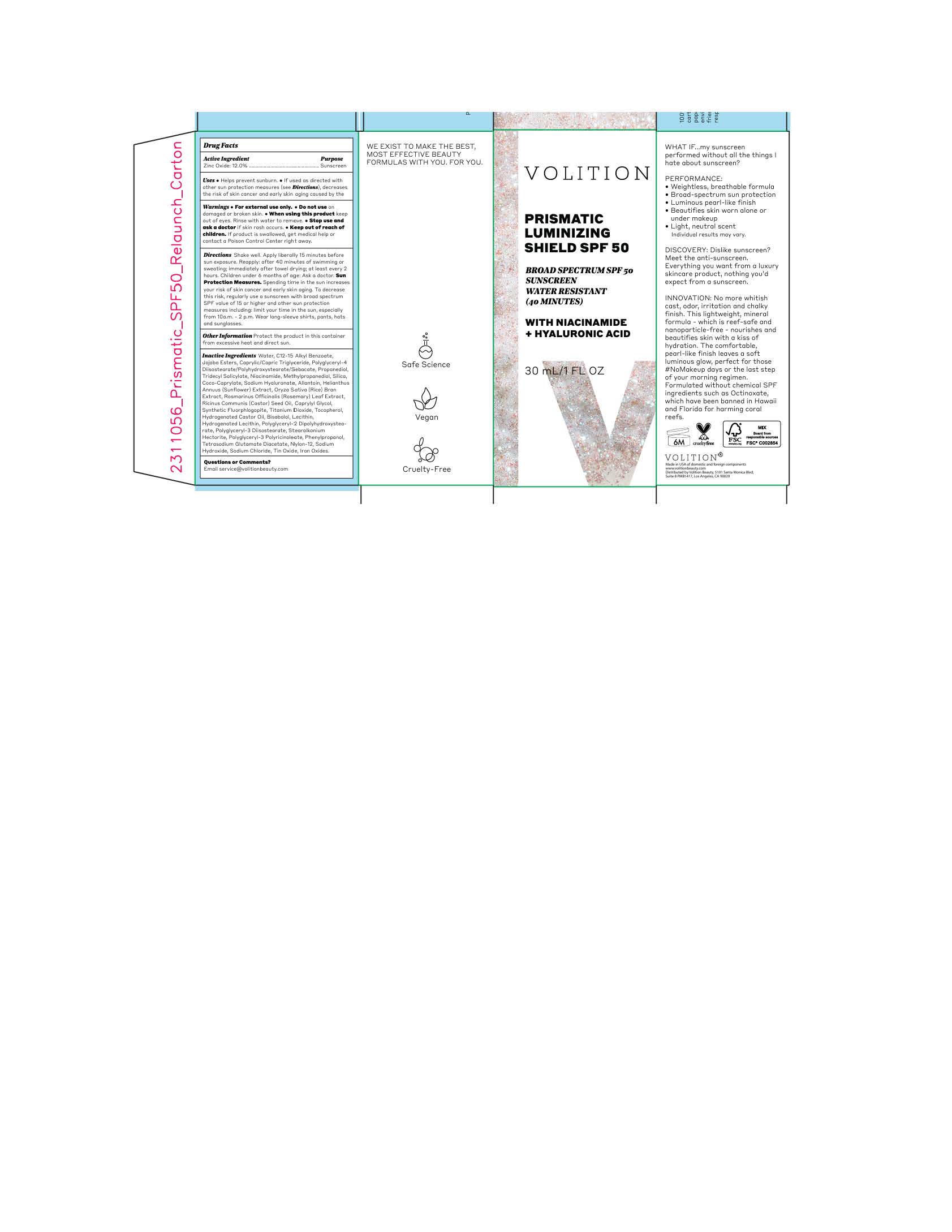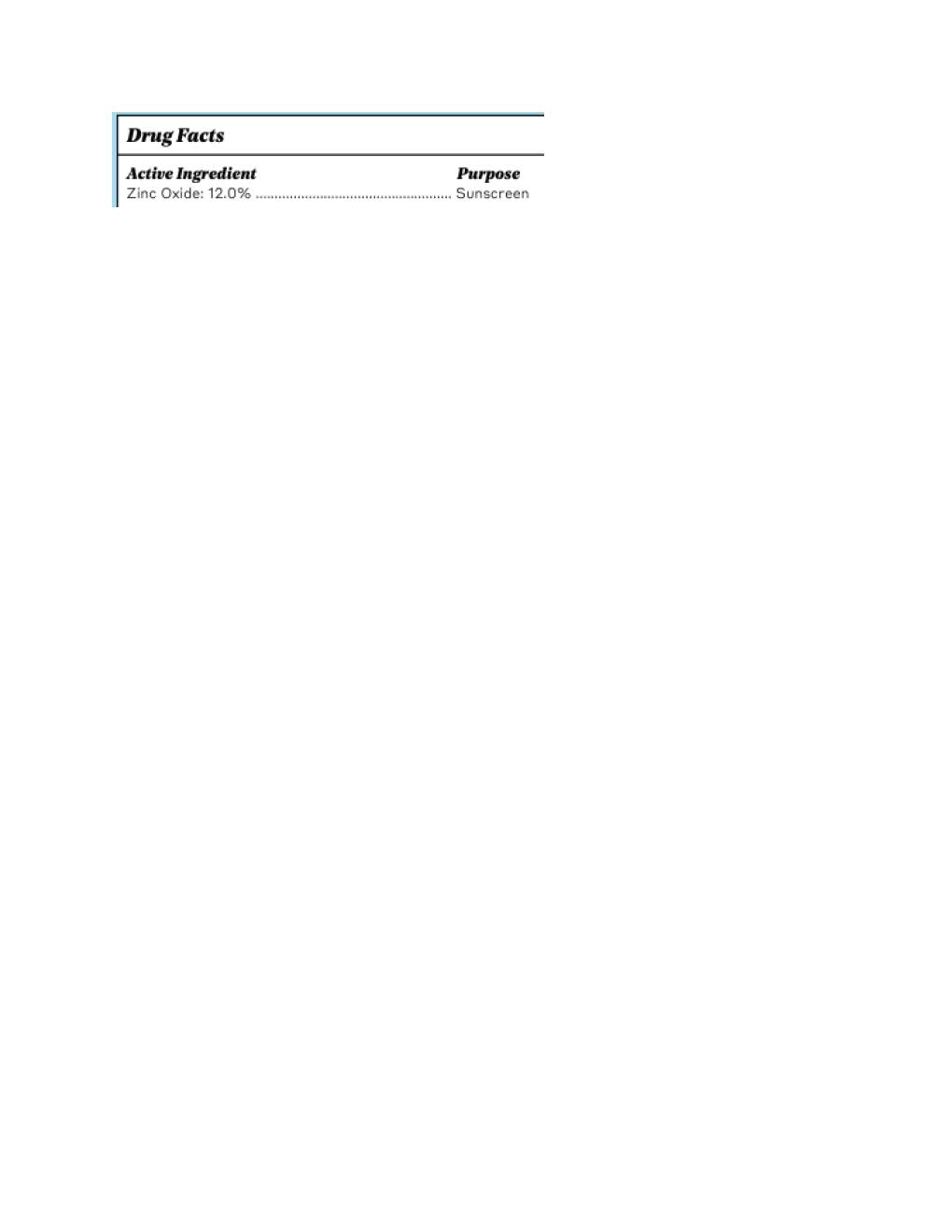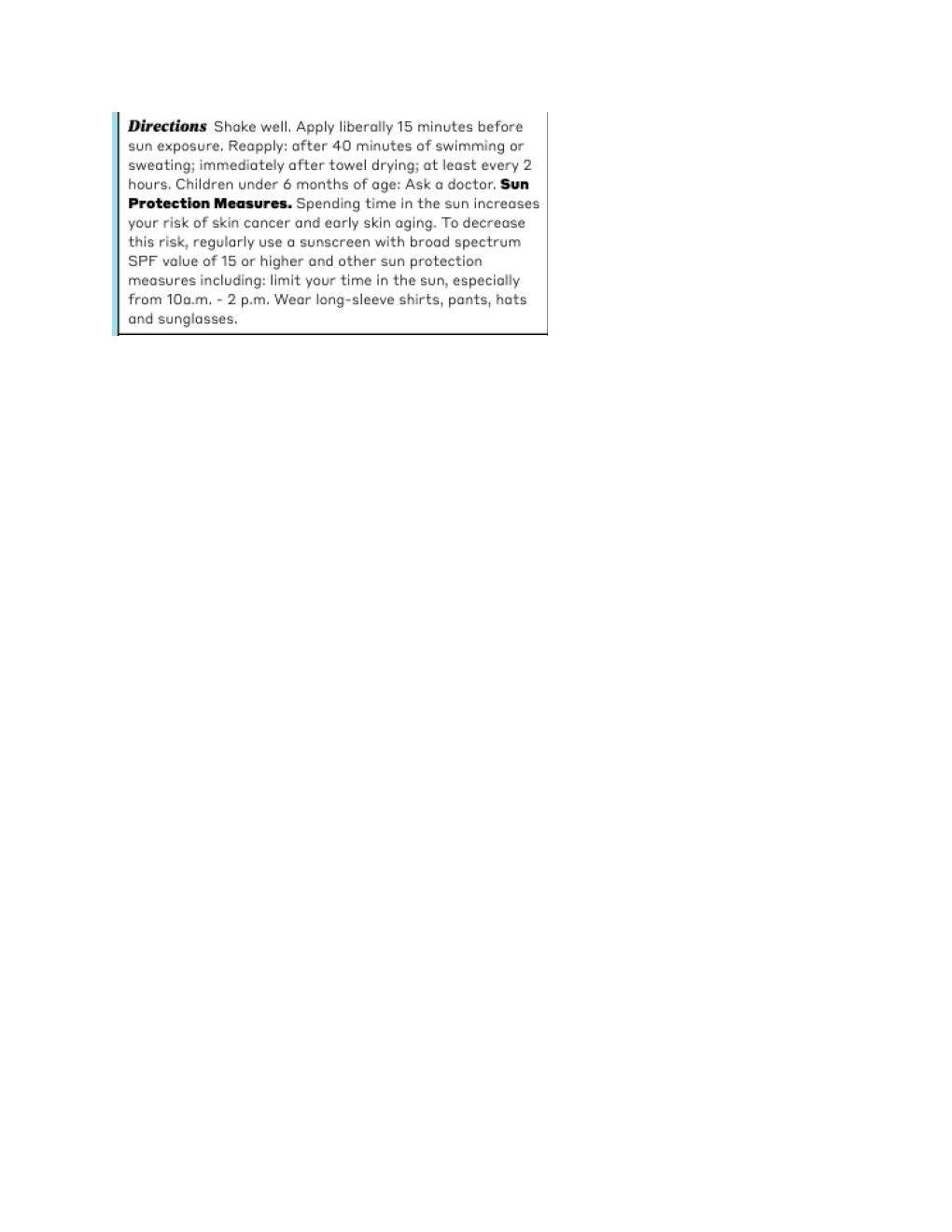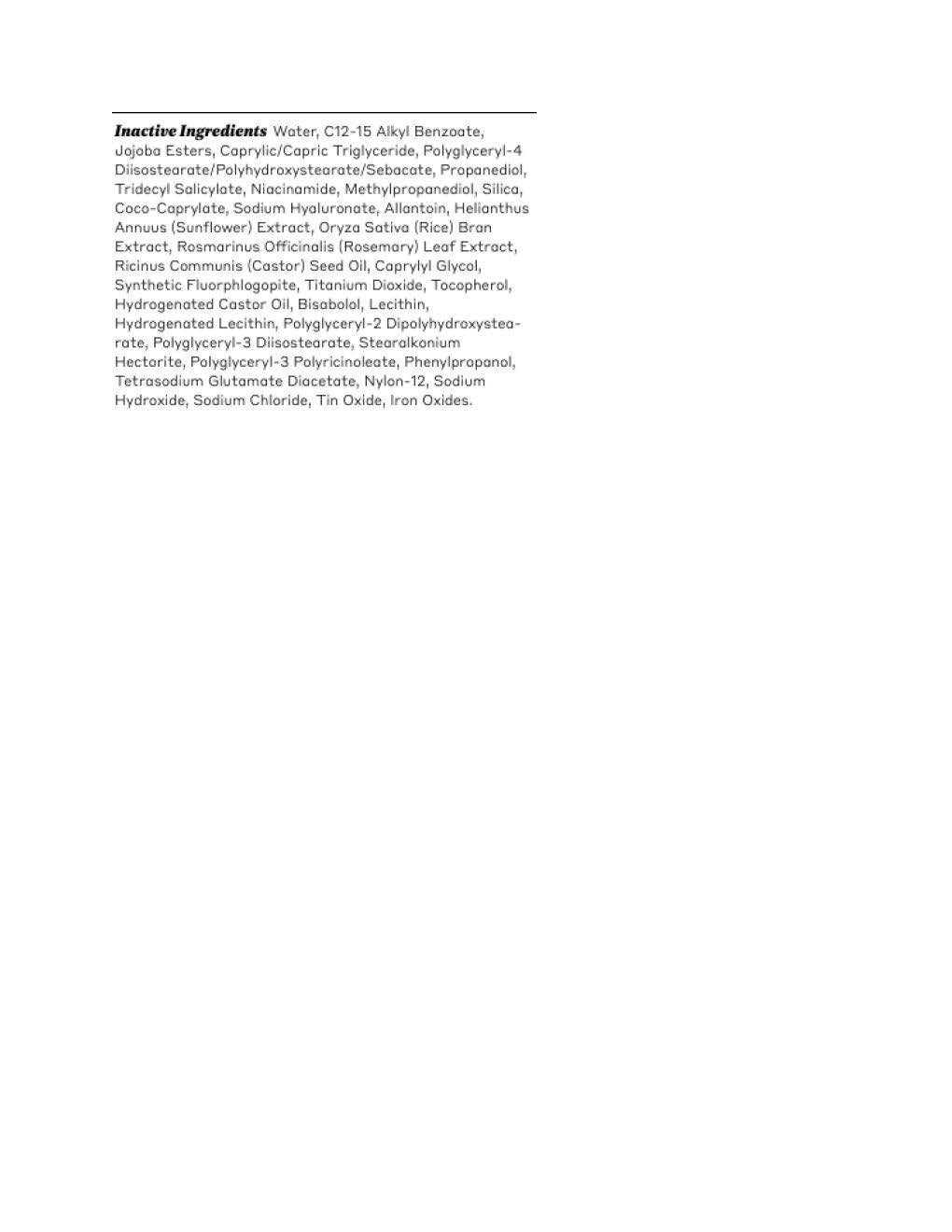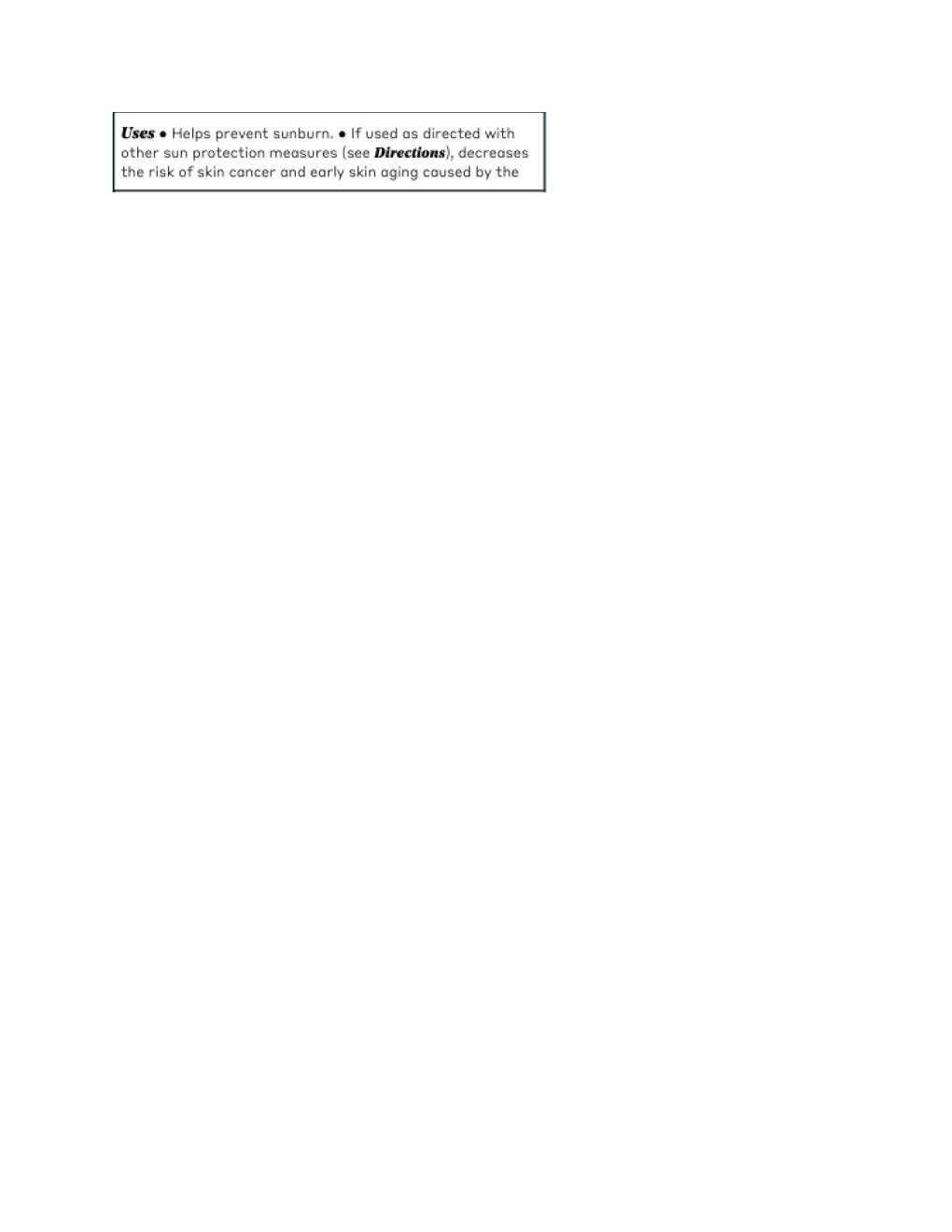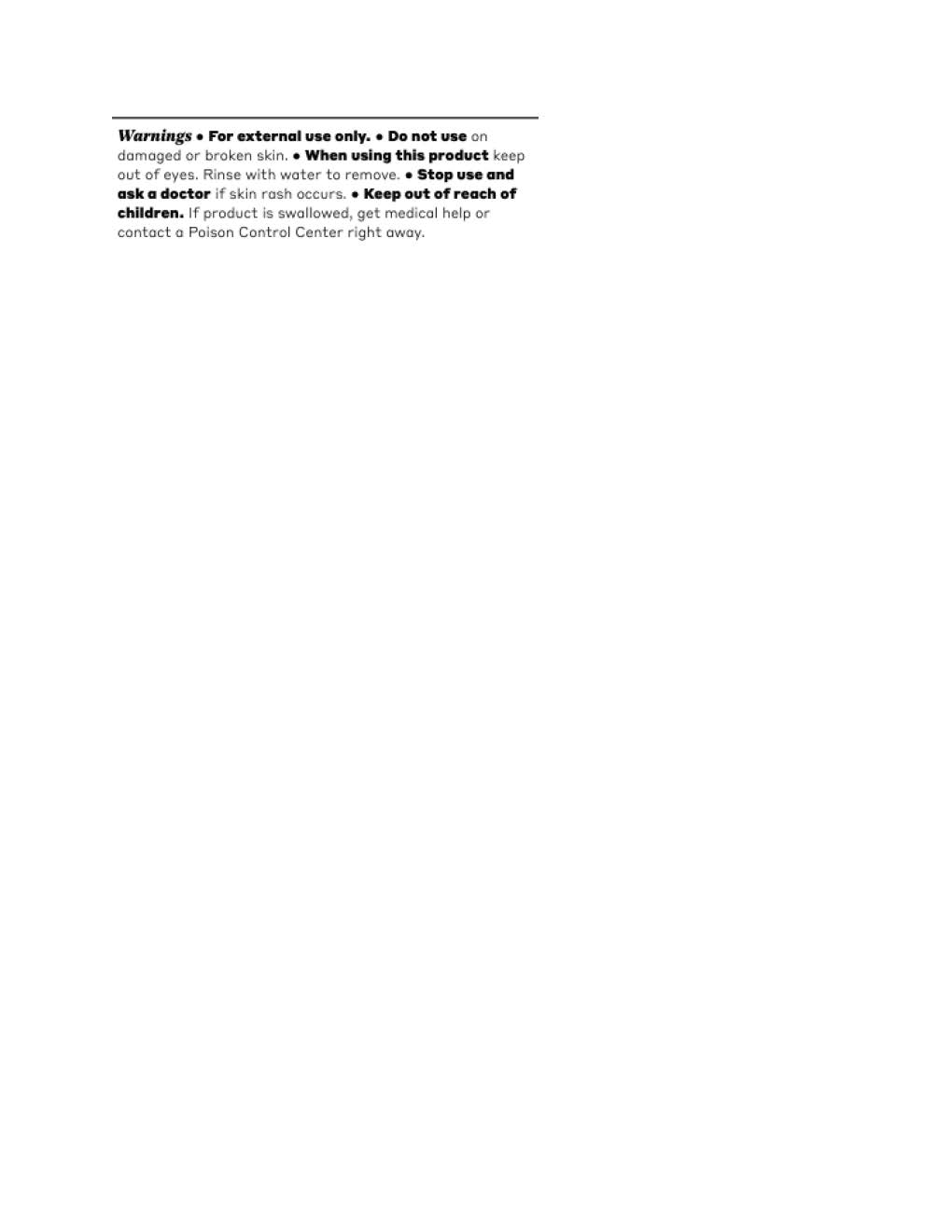 DRUG LABEL: Volition Prismatic Luminizing Shield
NDC: 72577-624 | Form: LOTION
Manufacturer: Volition
Category: otc | Type: HUMAN OTC DRUG LABEL
Date: 20250924

ACTIVE INGREDIENTS: ZINC OXIDE 132 mg/1 mL
INACTIVE INGREDIENTS: NIACINAMIDE; PROPANEDIOL; TETRASODIUM GLUTAMATE DIACETATE; SODIUM CHLORIDE; POLYGLYCERYL-4 DIISOSTEARATE/POLYHYDROXYSTEARATE/SEBACATE; FERROSOFERRIC OXIDE; HELIANTHUS ANNUUS FLOWERING TOP; LECITHIN, SOYBEAN; METHYLPROPANEDIOL; POLYGLYCERYL-2 DIPOLYHYDROXYSTEARATE; ALLANTOIN; ALKYL (C12-15) BENZOATE; ROSMARINUS OFFICINALIS FLOWERING TOP OIL; RICINUS COMMUNIS SEED; HYDROGENATED CASTOR OIL; STEARALKONIUM HECTORITE; JOJOBA OIL; ORYZA SATIVA WHOLE; TRIDECYL SALICYLATE; SILICON DIOXIDE; TOCOPHEROL; POLYGLYCERYL-3 DIISOSTEARATE; CAPRYLYL GLYCOL; COCO-CAPRYLATE; NYLON-12; PHENYLPROPANOL; FERRIC OXIDE RED; FERRIC OXIDE YELLOW; WATER; .ALPHA.-BISABOLOL, (+)-; SODIUM HYDROXIDE

Volition Prismatic Luminizing Shield